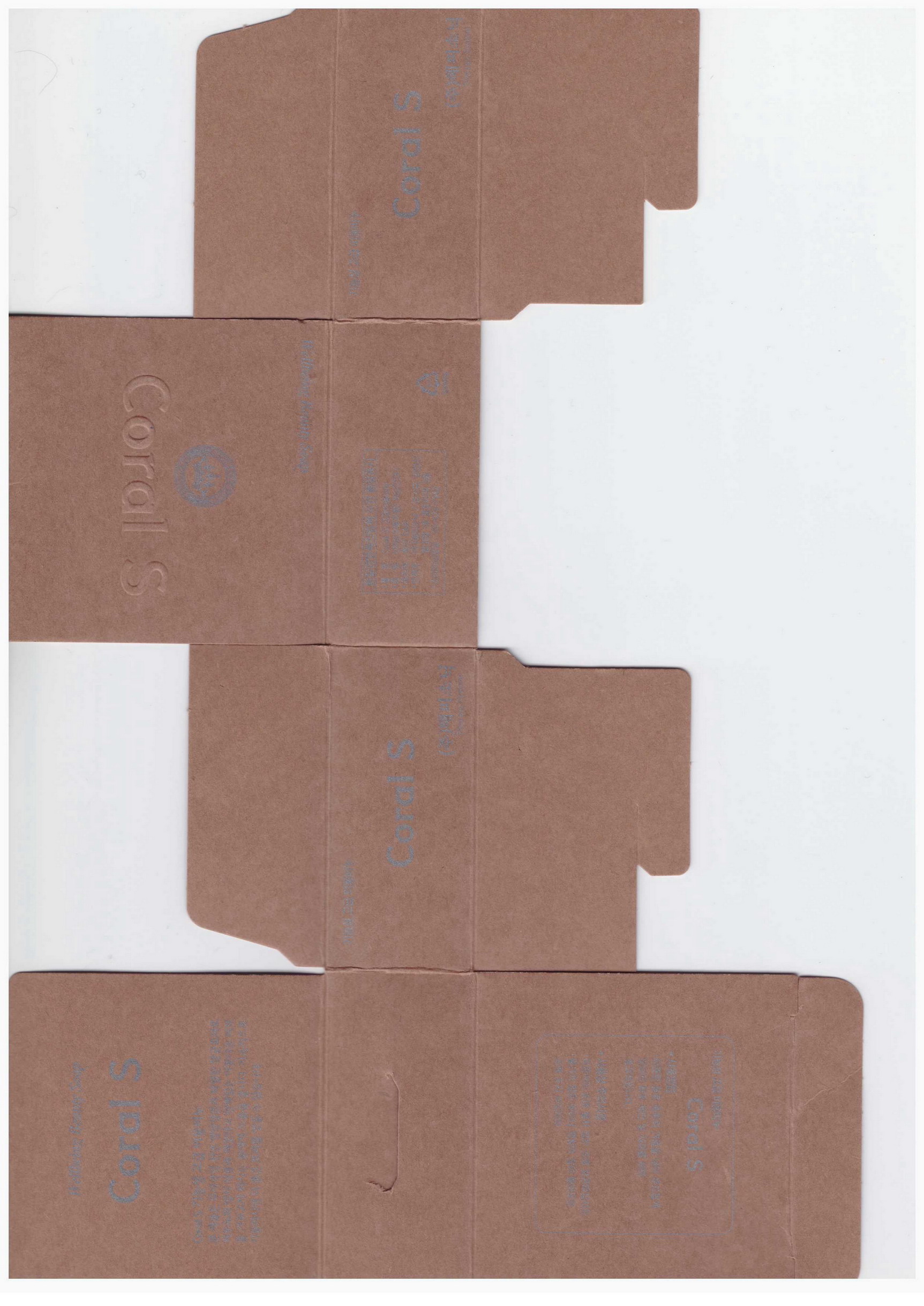 DRUG LABEL: Coral S
NDC: 61254-2001 | Form: SOAP
Manufacturer: Happy Sonic Global Co., Ltd.
Category: otc | Type: HUMAN OTC DRUG LABEL
Date: 20140302

ACTIVE INGREDIENTS: GLYCERIN 0.1 g/100 g
INACTIVE INGREDIENTS: COCONUT; PROPOLIS WAX; TITANIUM DIOXIDE

Drug Facts

ACTIVE INGREDIENT

glycerin

INACTIVE INGREDIENT

coconut soap chip, coral powder, titanium dioxide, edta-4na, lapa 5020, propolis, s-lact, jojoba oil, pg-4000, perfume

PURPOSE

skin protectant

keep out of reach of the children

INDICATIONS AND USAGE

apply every morning and night

WARNINGS

A. Please stop using the product in anyone of the following cases:
1) Rash, swelling, itching, irritation, and other abnormal reactions on the skin after using the product.
2) When the abnormalities above appear on the skin due to direct sunlight, etc.
B. Do NOT use on a scar, or skin affected by dermatitis, eczema, etc.
C. Notes for Storage
1) Make sure to close the lid after use.
2) Keep away from babies and children.
3) Do not store in high/low temperature or under direct sun light.
Abnormal products will be compensated for according to “Standard for Consumer Dispute Resolution” by Fair Trade Commission

DOSAGE AND ADMINISTRATION

for topical use only